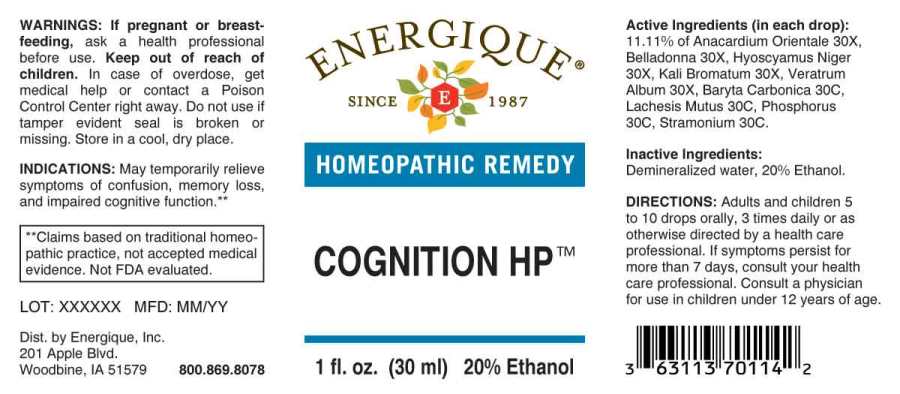 DRUG LABEL: Cognition
NDC: 44911-0583 | Form: LIQUID
Manufacturer: Energique, Inc.
Category: homeopathic | Type: HUMAN OTC DRUG LABEL
Date: 20241024

ACTIVE INGREDIENTS: SEMECARPUS ANACARDIUM JUICE 30 [hp_X]/1 mL; ATROPA BELLADONNA 30 [hp_X]/1 mL; HYOSCYAMUS NIGER 30 [hp_X]/1 mL; POTASSIUM BROMIDE 30 [hp_X]/1 mL; VERATRUM ALBUM ROOT 30 [hp_X]/1 mL; BARIUM CARBONATE 30 [hp_C]/1 mL; LACHESIS MUTA VENOM 30 [hp_C]/1 mL; PHOSPHORUS 30 [hp_C]/1 mL; DATURA STRAMONIUM 30 [hp_C]/1 mL
INACTIVE INGREDIENTS: WATER; ALCOHOL

DRUG FACTS:

ACTIVE INGREDIENTS:

(in each drop): 11.11% of Anacardium Orientale 30X, Belladonna 30X, Hyoscyamus Niger 30X, Kali Bromatum 30X, Veratrum Album 30X, Baryta Carbonica 30C, Lachesis Mutus 30C, Phosphorus 30C, Stramonium 30C.

INDICATIONS:

May temporarily relieve symptoms of confusion, memory loss, and impaired cognitive function.**

**Claims based on traditional homeopathic practice, not accepted medical evidence. Not FDA evaluated.

WARNINGS:

If pregnant or breast-feeding, ask a health professional before use.

Keep out of reach of children. In case of overdose, get medical help or contact a Poison Control Center right away.

Do not use if tamper evident seal is broken or missing. Store in a cool, dry place.

Keep out of reach of children. In case of overdose, get medical help or contact a Poison Control Center right away.

DIRECTIONS:

Adults and children 5 to 10 drops orally, 3 times daily or as otherwise directed by a health care professional. If symptoms persist for more than 7 days, consult your health care professional. Consult a physician for use in children under 12 years of age.

INDICATIONS:

May temporarily relieve symptoms of confusion, memory loss, and impaired cognitive function.**

**Claims based on traditional homeopathic practice, not accepted medical evidence. Not FDA evaluated.

INACTIVE INGREDIENTS:

Demineralized water, 20% Ethanol.

QUESTIONS:

Dist. by Energique, Inc.

201 Apple Blvd

Woodbine, IA 51579 800.869.8078

PACKAGE LABEL DISPLAY:

ENERGIQUE

SINCE 1987

HOMEOPATHIC REMEDY

COGNITION HP

1 fl. oz. (30 ml)